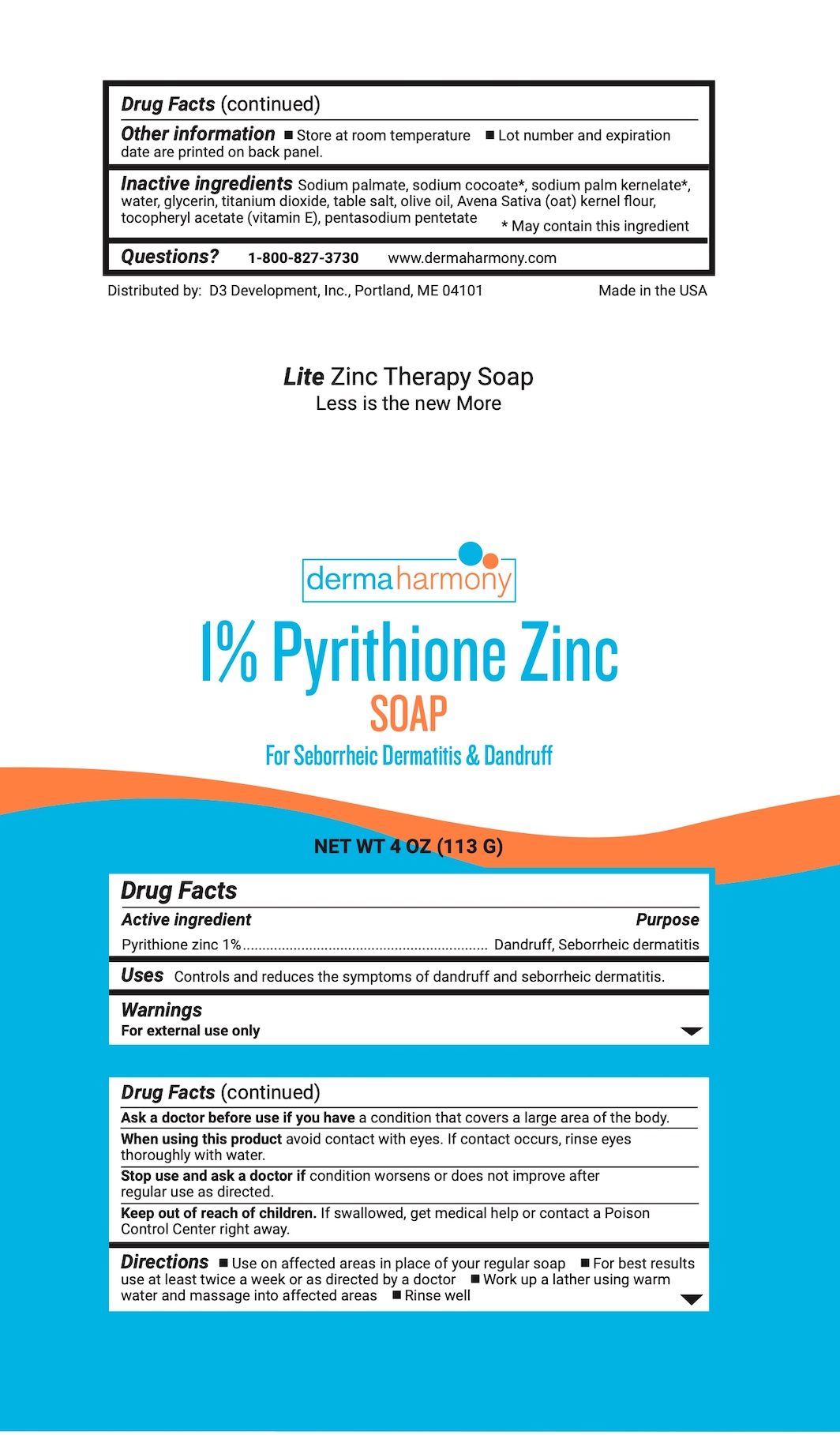 DRUG LABEL: Dermaharmony 1% Pyrithione Zinc
NDC: 71819-010 | Form: SOAP
Manufacturer: D3 Development, Inc.
Category: otc | Type: HUMAN OTC DRUG LABEL
Date: 20251202

ACTIVE INGREDIENTS: PYRITHIONE ZINC 1 g/100 g
INACTIVE INGREDIENTS: SODIUM PALM KERNELATE; OLIVE OIL; SODIUM PALMATE; .ALPHA.-TOCOPHEROL ACETATE, D-; PENTASODIUM PENTETATE; SODIUM CHLORIDE; TITANIUM DIOXIDE; WATER; SODIUM COCOATE; GLYCERIN; OATMEAL

Pyrithione Zinc 1% Bar

Drug Facts

Active ingredient

Pyrithione zinc 1%

Purpose

Dandruff, Seborrheic dermatitis

Uses

Controls and reduces the symptoms of dandruff and seborrheic dermatitis.

Warnings

For external use only

Ask a doctor before use if you havea condition that covers a large area of the body.

WHEN USING

When using this productavoid contact with eyes. If contact occurs, rinse eyes thoroughly with water.

Stop use and ask a doctor ifcondition worsens or does not improve after regular use as directed.

Keep out of reach of children.If swallowed, get medical help or contact a Poison Control Center right away.

Directions

- Use on affected areas in place of your regular soap
- For best results use at least twice a week or as directed by a doctor
- Work up a lather using warm water and massage into affected areas
- Rinse well

Other information

- Store at room temperature
- Lot number and expiration date are printed on back panel.

Inactive ingredients

Sodium palmate, sodium cocoate*, sodium palm kernelate*, water, glycerin, titanium dioxide, table salt, olive oil, Avena Sativa (oat) kernel flour, tocopheryl acetate (vitamin E), pentasodium pentetate

*May contain this ingredient

Questions?

1-800-827-3730

www.dermaharmony.com

Distributed by:

D3 Development, Inc., Portland, ME 04101

Made in the USA

PACKAGE LABEL

dermaharmony

1% Pyrithione Zinc SOAP

For Seborrheic Dermatitis & Dandruff

NET WT 4.0 OZ (113 G)